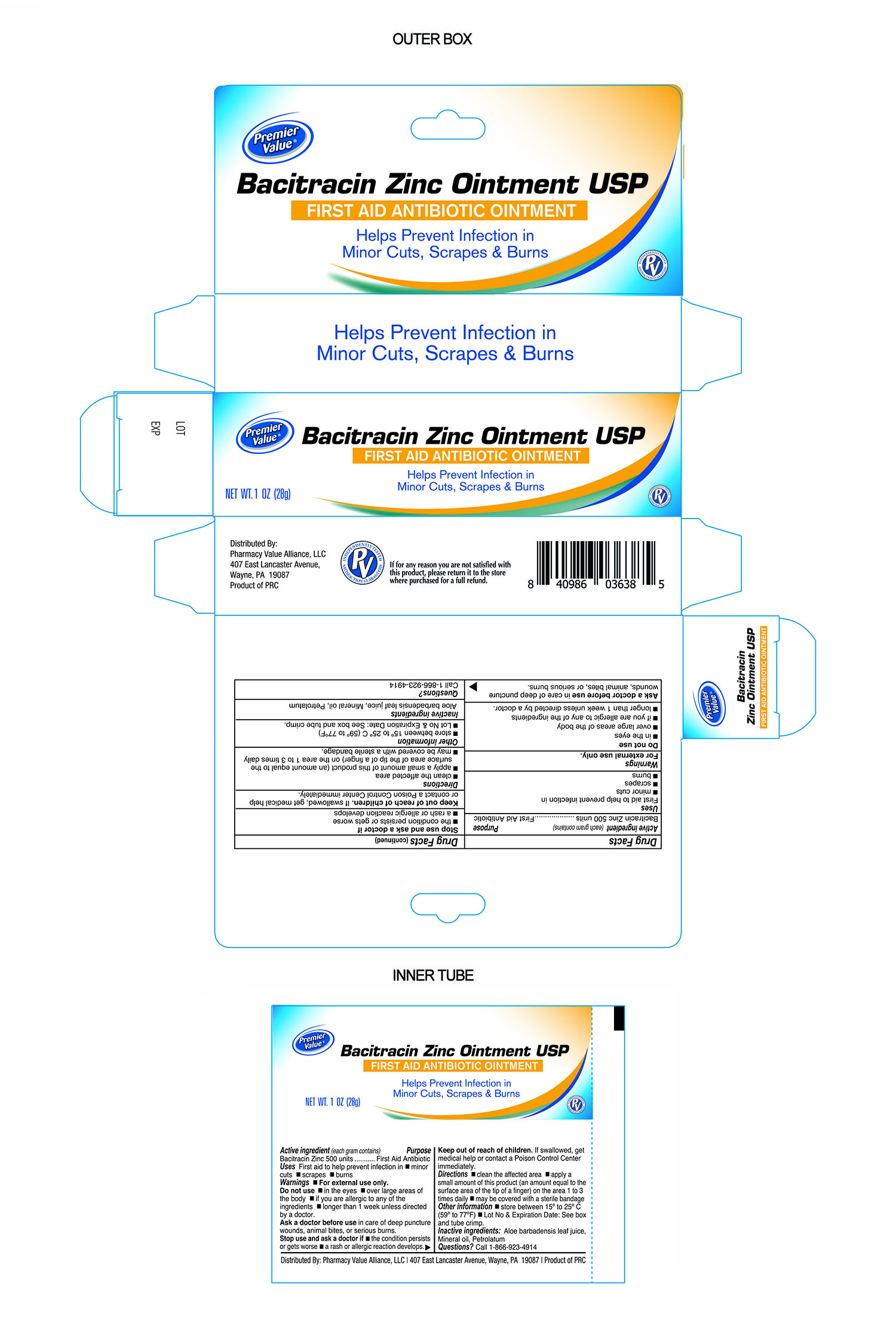 DRUG LABEL: Premier Value Bacitracin Zinc
NDC: 68016-107 | Form: OINTMENT
Manufacturer: Pharmacy Value Alliance LLC
Category: otc | Type: HUMAN OTC DRUG LABEL
Date: 20241220

ACTIVE INGREDIENTS: BACITRACIN ZINC 500 [USP'U]/1 g
INACTIVE INGREDIENTS: LIGHT MINERAL OIL; PETROLATUM; ALOE VERA LEAF

Premier Value Bacitracin Zinc Ointment USP

Active Ingredient

Bacitracin Zinc 500 Units per gram

Purpose

First Aid Antibiotic

Uses

First Aid to help prevent infection in

- minor cuts
- scrapes
- burns

Warnings

For External Use Only.

Do Not Use

- in eyes
- over large areas of the body
- if you are allergic to ay of the ingredients
- longer than 1 week unless directed by a doctor

Ask Doctor before Use

In care of deep puncture wounds, animal bites, or serious burns.

Stop Use and Ask Doctor if

- The condition persists or gets worse
- A rash or allergic reaction develops

Directions

- Clean the affected area
- Apply a small amount of this product (an amount equal to the surface area of the tip of a finger) on the area 1 to 3 times daily
- May be covered with a sterile bandage

Inactive Ingredients

Aloe barbadensis leaf juice, mineral oil, petrolatum

Questions

Call 1-866-923-4914

If for any reason you are not satisfied with this product, please return it to the store where purchased for a full refund.

Keep out of reach of children

If swallowed, get medical help or contact a Poison Control Center immediately

Other Information

Store Between 15° to 25°C (59° to 77°F)

Distributed By:

Pharmacy Value Alliance, LLC.

407 East Lancaster Avenue,

Wayne, PA. 19087

Product of PRC